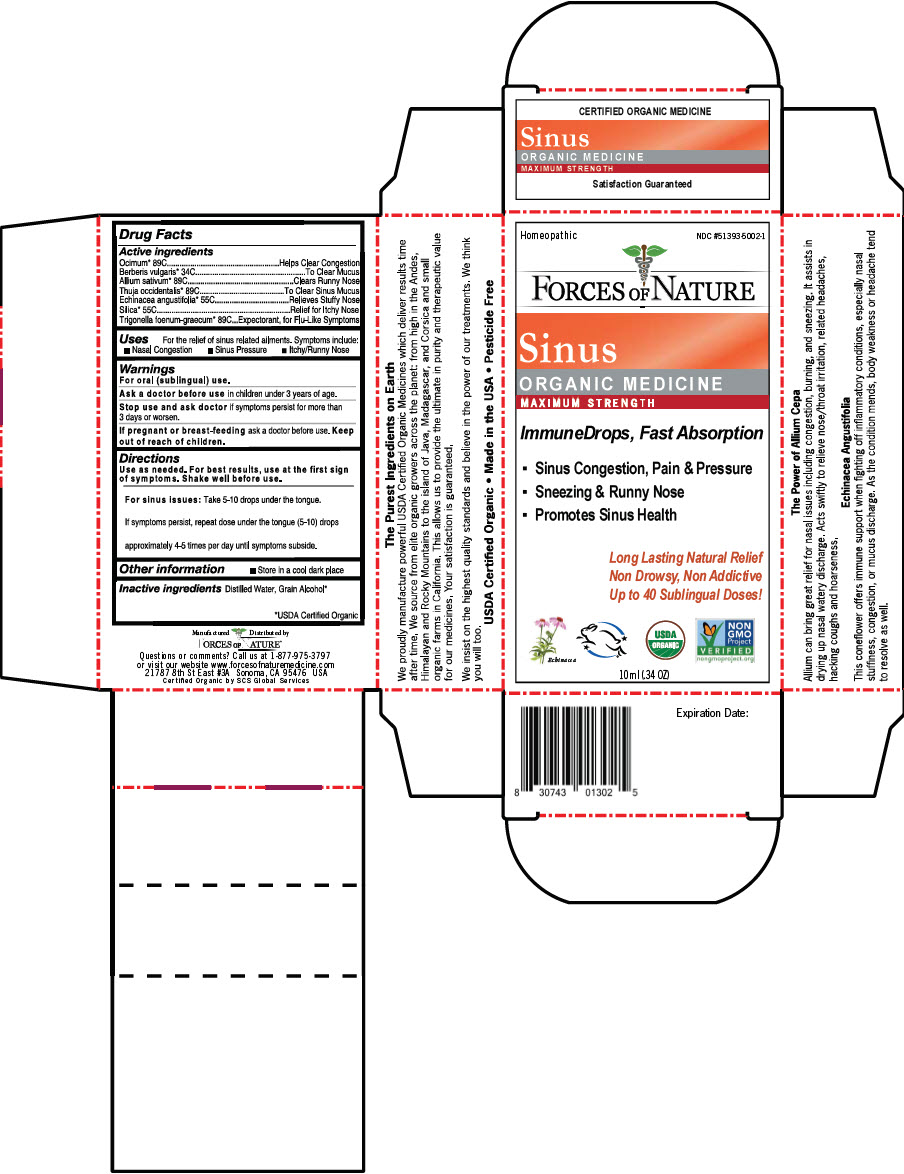 DRUG LABEL: Sinus
NDC: 51393-5002 | Form: SOLUTION/ DROPS
Manufacturer: Forces of Nature
Category: homeopathic | Type: HUMAN OTC DRUG LABEL
Date: 20210928

ACTIVE INGREDIENTS: HOLY BASIL LEAF 89 [hp_C]/100 mL; BERBERIS VULGARIS ROOT 34 [hp_C]/100 mL; GARLIC 89 [hp_C]/100 mL; THUJA OCCIDENTALIS LEAF 89 [hp_C]/100 mL; ECHINACEA ANGUSTIFOLIA ROOT 55 [hp_C]/100 mL; SILICON DIOXIDE 55 [hp_C]/100 mL
INACTIVE INGREDIENTS: Water; Alcohol

Sinus
Maximum Strength

Drug Facts

ACTIVE INGREDIENT

PURPOSE

Active ingredients
Ocimum [USDA Certified Organic] 89C | Helps Clear Congestion
Berberis vulgaris 34C | To Clear Mucus
Allium sativum 89C | Clears Runny Nose
Thuja occidentalis 89C | To Clear Sinus Mucus
Echinacea angustifolia 55C | Relieves Stuffy Nose
Silica 55C | Relief for Itchy Nose
Trigonella foenum-graecum 89C | Expectorant, for Flu-Like Symptoms

Uses

For the relief of sinus related ailments. Symptoms include:

- Nasal Congestion
- Sinus Pressure
- Itchy/Runny Nose

Warnings

For oral (sublingual) use.

Ask a doctor before use in children under 3 years of age.

Stop use and ask doctor if symptoms persist for more than 3 days or worsen.

PREGNANCY OR BREAST FEEDING

If pregnant or breast-feeding ask a doctor before use.

Keep out of reach of children.

Directions

Use as needed. For best results, use at the first sign of symptoms. Shake well before use.

For sinus issues

Take 5-10 drops under the tongue.

If symptoms persist, repeat dose under the tongue (5-10) drops approximately 4-5 times per day until symptoms subside.

Other information

- Store in a cool dark place

Inactive ingredients

Distilled Water, Grain Alcohol

Questions or comments?

Call us at 1-877-975-3797 or visit our website www.forcesofnaturemedicine.com

Manufactured Distributed by
FORCES OF NATURE®
21787 8th St East #3A Sonoma, CA 95476 USA

PRINCIPAL DISPLAY PANEL - 10 ml Bottle Carton

Homeopathic
NDC #51393-5002-1

FORCES OF NATURE

Sinus
ORGANIC MEDICINE
MAXIMUM STRENGTH

ImmuneDrops, Fast Absorption

- Sinus Congestion, Pain & Pressure
- Sneezing & Runny Nose
- Promotes Sinus Health

Long Lasting Natural Relief
Non Drowsy, Non Addictive
Up to 40 Sublingual Doses!

Echinacea

USDA
ORGANIC

NON
GMO
Project
VERIFIED
nongmoproject.org

10 ml (.34 OZ)